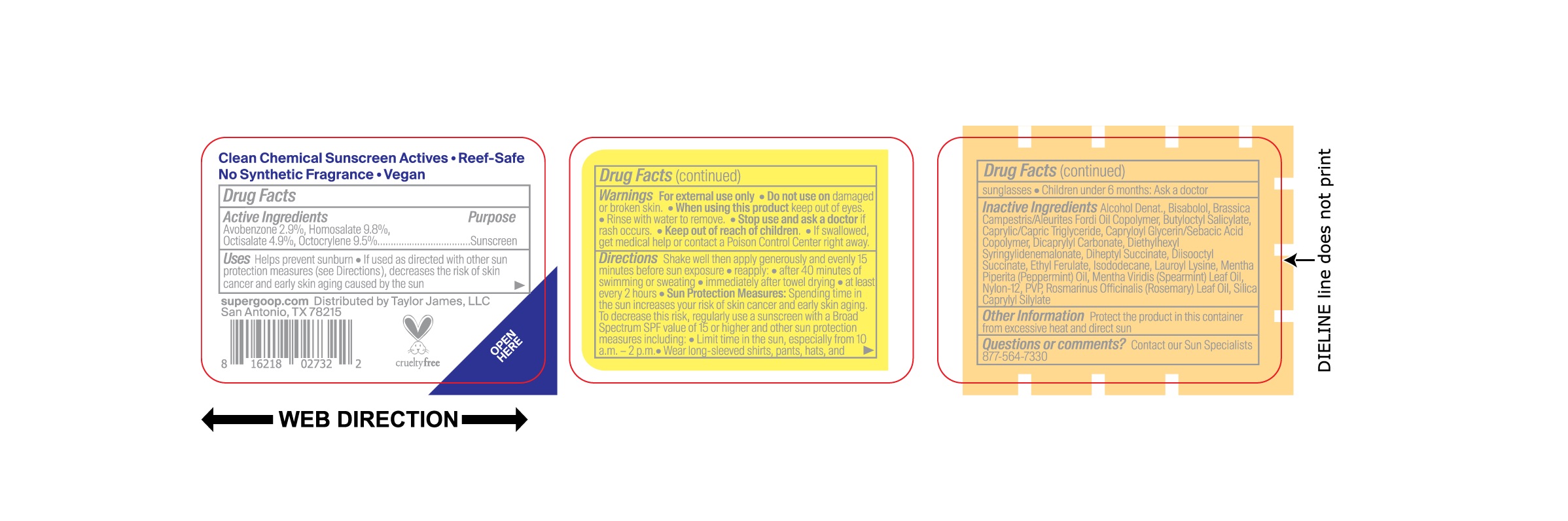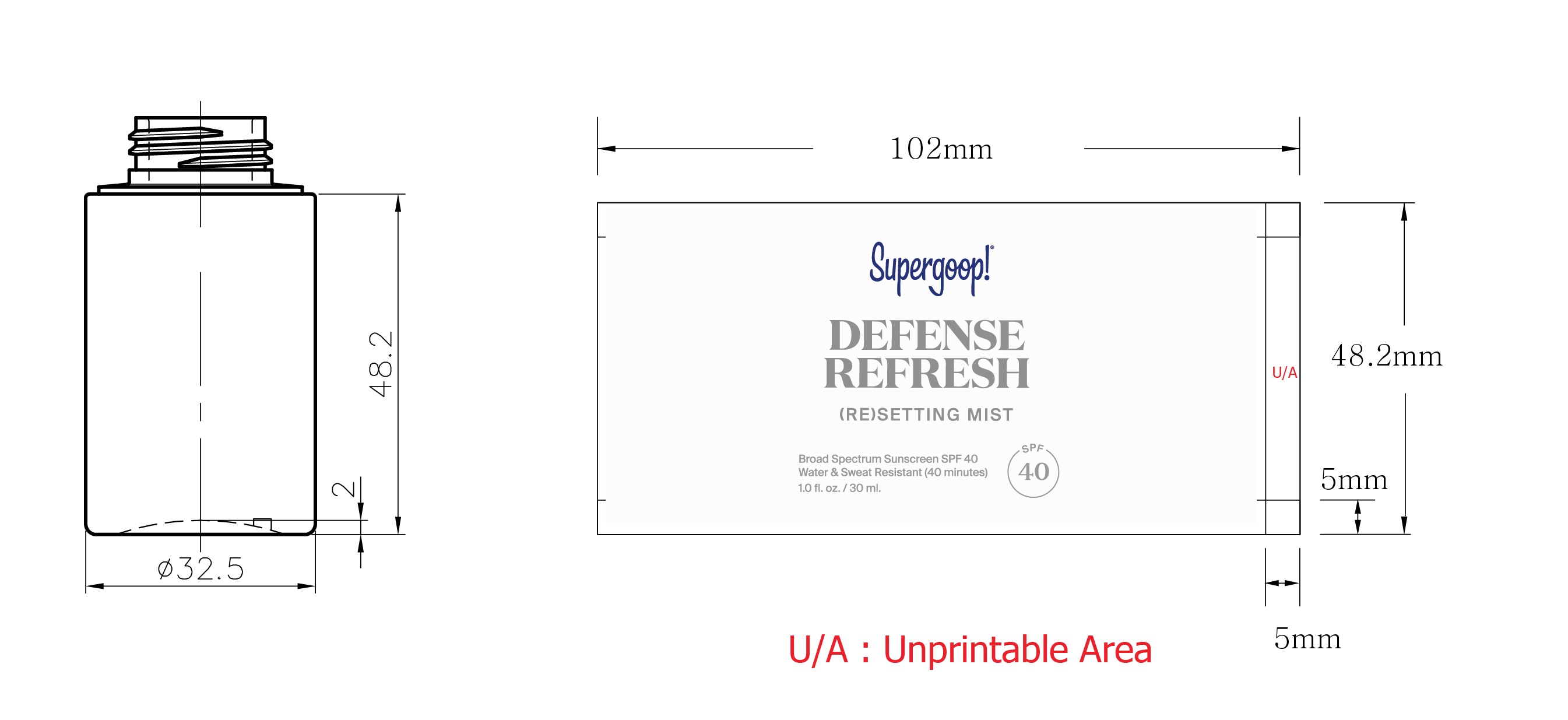 DRUG LABEL: Defense Refresh (Re)Setting Mist SPF 40
NDC: 75936-354 | Form: LIQUID
Manufacturer: Supergoop LLC
Category: otc | Type: HUMAN OTC DRUG LABEL
Date: 20241204

ACTIVE INGREDIENTS: HOMOSALATE 9.8 g/100 mL; AVOBENZONE 2.9 g/100 mL; OCTISALATE 4.9 g/100 mL; OCTOCRYLENE 9.5 g/100 mL
INACTIVE INGREDIENTS: ALCOHOL; BUTYLOCTYL SALICYLATE; DICAPRYLYL CARBONATE; DIETHYLHEXYL SYRINGYLIDENEMALONATE; DIHEPTYL SUCCINATE; ETHYL FERULATE; ISODODECANE; PEPPERMINT OIL; SPEARMINT OIL; ROSEMARY OIL; NYLON-12; POVIDONE, UNSPECIFIED; LEVOMENOL; MEDIUM-CHAIN TRIGLYCERIDES; CAPRYLOYL GLYCERIN/SEBACIC ACID COPOLYMER (2000 MPA.S); LAUROYL LYSINE

Defense Refresh (Re)Setting Mist SPF 40

ACTIVE INGREDIENT

Avobenzone 2.9%..............Sunscreen

Homosalate 9.8%.............Sunscreen

Octisalate 4.9%..................Sunscreen

Octocrylene 9.5%...............Sunscreen

PURPOSE

Helps prevent sunburn.

If used as directed with other sun protection measures (see Directions), decreases the risk of skin cancer and early skin aging caused by the sun

Keep out of reach of children. If swallowed, get medical help or contact a Poison Control Center right away.

Stop use and ask a doctor if rash occurs.

WARNINGS

For external use only. Do not useon damaged or broken skin. When using this product keep out of eyes. Rinse with water to remove.

DOSAGE AND ADMINISTRATION

· Shake well then apply generously and evenly 15 minutes before sun exposure.

· reapply:

· after 40 minutes of swimming or sweating

· immediately after towel drying

· at least every 2 hours

· Sun Protection Measures: spending time in the sun increases your risk of skin cancer and early skin aging. To decrease this risk, regularly use a sunscreen with a Broad Spectrum SPF value of 15 or higher and other sun protection measures including:

· Limit time in the sun, especially from 10 a.m. - 2 p.m.

· Wear long-sleeved shirts, pants, hats, and sunglasses

· Children under 6 months: Ask a doctor

INACTIVE INGREDIENT

Alcohol Denat., Bisabolol, Brassica Campestris/Aleurites Fordi Oil Copolymer, Butyloctyl Salicylate, Caprylic/Capric Triglyceride, Capryloyl Glycerin/Sebacic Acid Copolymer, Dicaprylyl Carbonate, Diethylhexyl Syringylidenemalonate, Diheptyl Succinate, Diisooctyl Succinate, Ethyl Ferulate, Isododecane, Lauroyl Lysine, Mentha Piperita (Peppermint) Oil, Mentha Viridis (Spearmint) Leaf Oil, Nylon-12, PVP, Rosmarinus Officinalis (Rosemary) Leaf Oil, Silica Caprylyl Silylate

OTHER SAFETY INFORMATION

Protect the product in this contianer from excessive heat and direct sun.

PACKAGE LABEL

Supergoop!

Defense Refresh

(RE) Setting Mist

SPF 40

Broad Spectrum Sunscreen SFP 40

Water & Sweat Resistant (40 minutes)

1.0 fl. oz. / 30 ml.